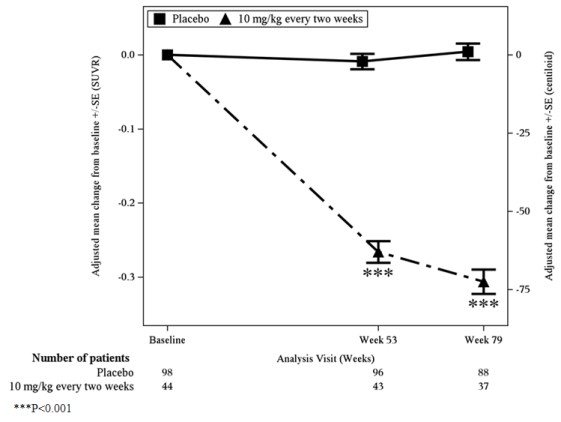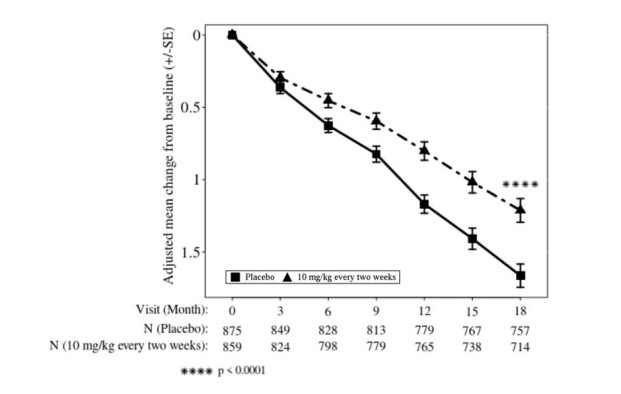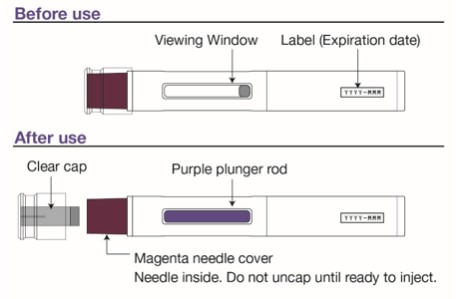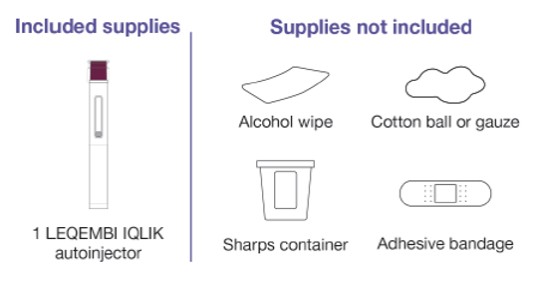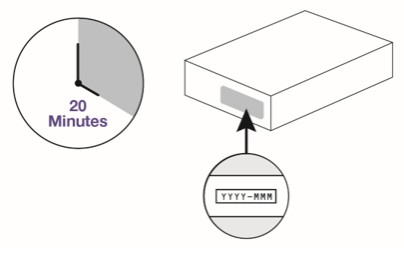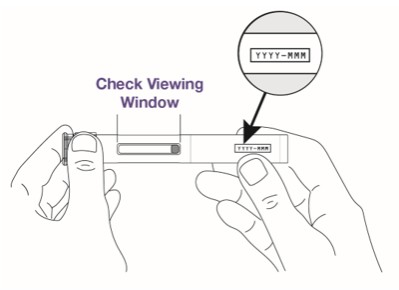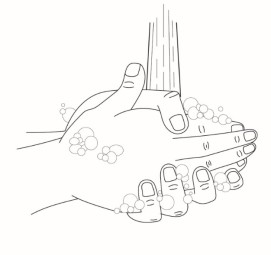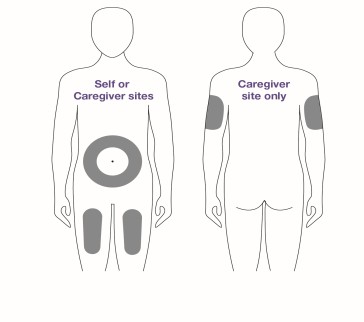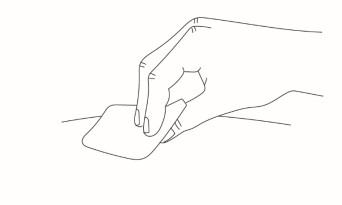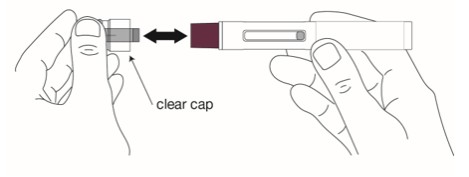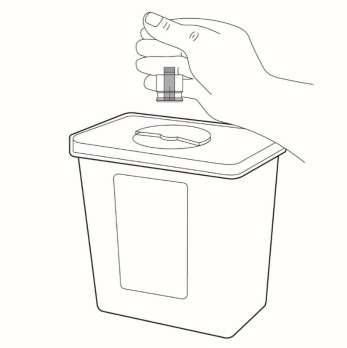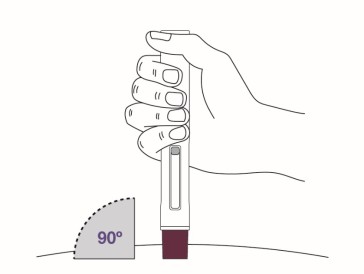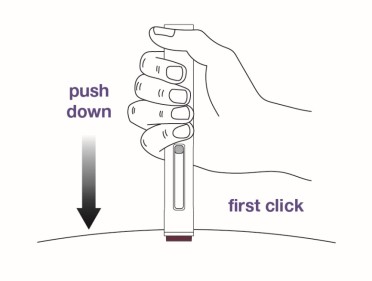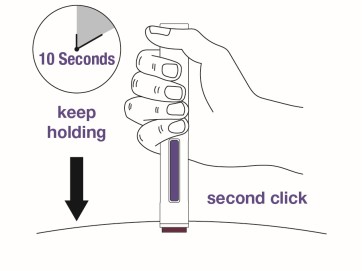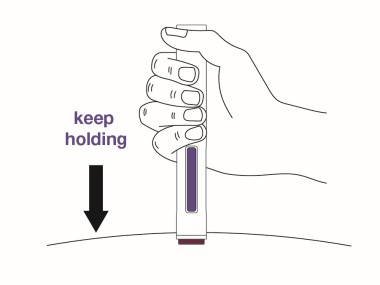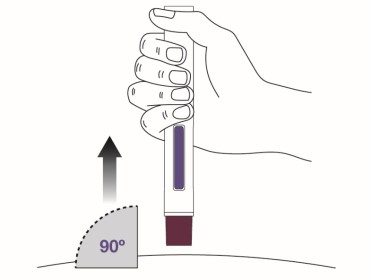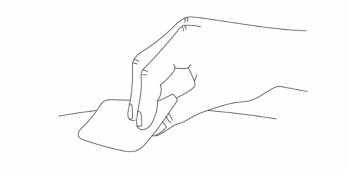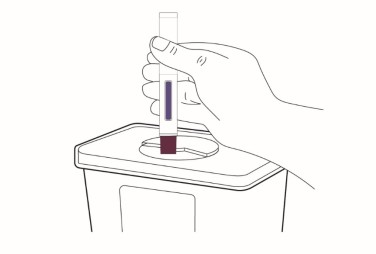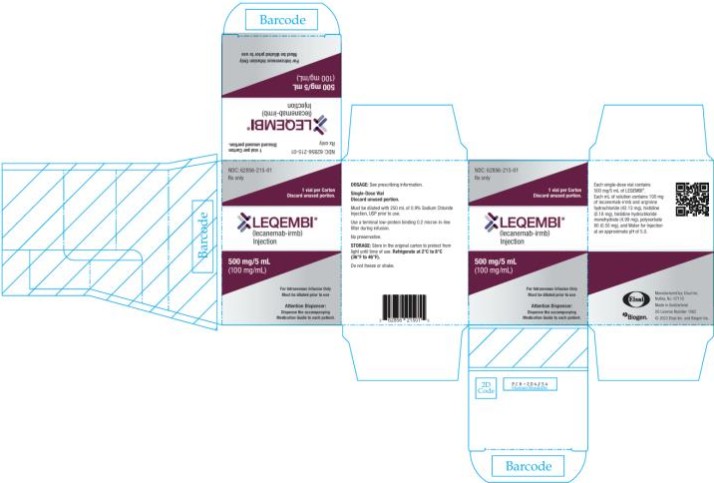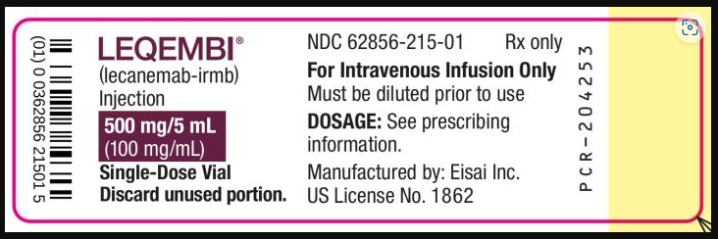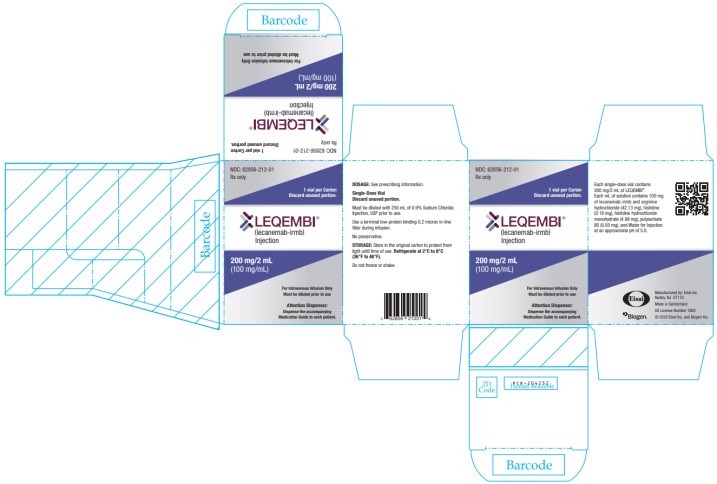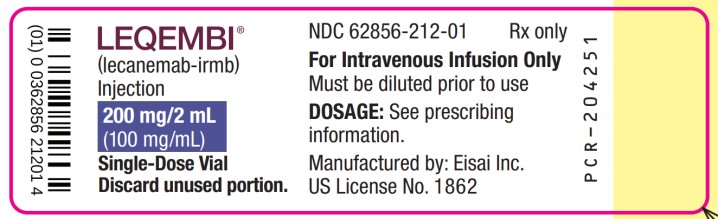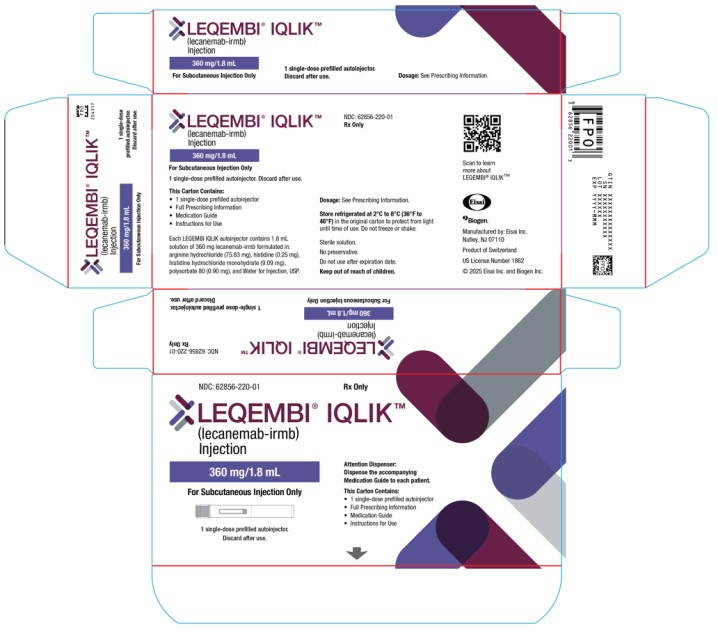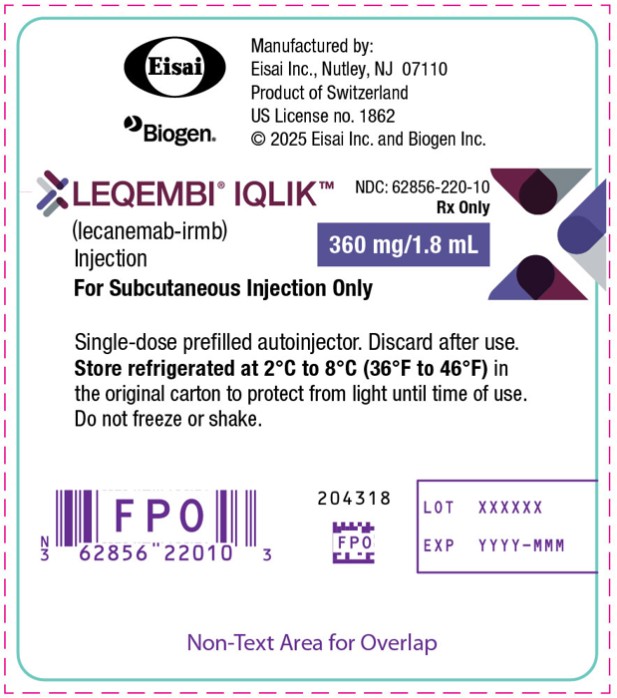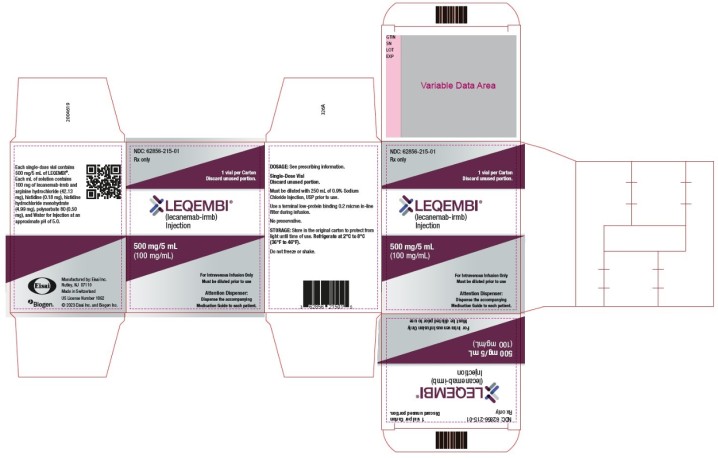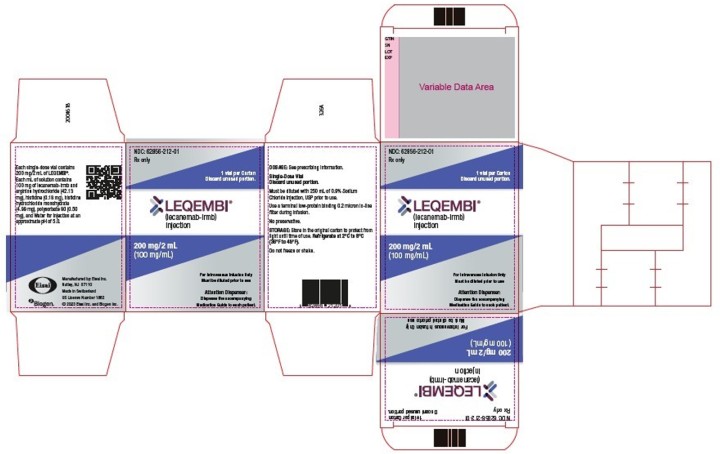 DRUG LABEL: LEQEMBI
NDC: 62856-215 | Form: INJECTION, SOLUTION
Manufacturer: Eisai Inc.
Category: prescription | Type: HUMAN PRESCRIPTION DRUG LABEL
Date: 20260123

ACTIVE INGREDIENTS: LECANEMAB 100 mg/1 mL
INACTIVE INGREDIENTS: ARGININE HYDROCHLORIDE 42.13 mg/1 mL; HISTIDINE 0.18 mg/1 mL; HISTIDINE MONOHYDROCHLORIDE MONOHYDRATE 4.99 mg/1 mL; POLYSORBATE 80 0.50 mg/1 mL; WATER

HIGHLIGHTS OF PRESCRIBING INFORMATION

These highlights do not include all the information needed to use LEQEMBI® safely and effectively. See full prescribing information for LEQEMBI®.
LEQEMBI® (lecanemab-irmb) injection, for intravenous or subcutaneous use
Initial U.S. Approval: 2023

RECENT MAJOR CHANGES

Dosage and Administration (2.2, 2.3, 2.4, 2.5, 2.6, 2.7) | 8/2025
Contraindications (4) | 8/2025
Warnings and Precautions (5.1) | 12/2025
Warnings and Precautions (5.2, 5.3) | 8/2025

WARNING: AMYLOID RELATED IMAGING ABNORMALITIES

See full prescribing information for complete boxed warning.

Monoclonal antibodies directed against aggregated forms of beta amyloid, including LEQEMBI, can cause amyloid related imaging abnormalities (ARIA), as ARIA with edema (ARIA-E) and ARIA with hemosiderin deposition (ARIA-H). ARIA is usually asymptomatic, although serious and life-threatening events can occur. ARIA can be fatal. Serious intracerebral hemorrhages > 1 cm have occurred in patients treated with this class of medications. ARIA-E can cause focal neurologic deficits that can mimic ischemic stroke. (5.1, 6.1)

ApoE ε4 Homozygotes

Patients treated with this class of medications, including LEQEMBI, who are ApoE ε4 homozygotes have a higher incidence of ARIA, including symptomatic and serious ARIA, compared to heterozygotes and noncarriers. Testing for ApoE ε4 status should be performed prior to initiation of treatment to inform the risk of developing ARIA. Prior to testing, the risk of ARIA across genotypes and implications of genetic testing results should be discussed with patients. (5.1)

Consider the benefit for the treatment of Alzheimer’s disease and risk of ARIA when deciding to treat with LEQEMBI. (5.1, 14)

1 INDICATIONS AND USAGE

LEQEMBI is an amyloid beta-directed antibody indicated for the treatment of Alzheimer’s disease. Treatment with LEQEMBI should be initiated in patients with mild cognitive impairment or mild dementia stage of disease, the population in which treatment was initiated in clinical trials. (1)

2 DOSAGE AND ADMINISTRATION

- Confirm the presence of amyloid beta pathology prior to initiating treatment. (2.1)
- Obtain a recent baseline brain MRI prior to initiating treatment. (2.4, 5.1)
- Obtain an MRI within approximately one week prior to the 3rd, 5th, 7th, and 14th infusions. If radiographically observed ARIA occurs, treatment recommendations are based on type, severity, and presence of symptoms. (2.4, 5.1)
- Recommended starting dosage: 10 mg/kg once every 2 weeks administered after dilution as an intravenous infusion over approximately one hour. (2.2)
- After 18 months, continue treatment once every 2 weeks or transition to an intravenous or subcutaneous maintenance dosage. (2.2)
- Recommended maintenance dosage:
  - Intravenous infusion: 10 mg/kg once every 4 weeks (2.2, 2.5)
  - Subcutaneous injection: 360 mg administered once a week using the LEQEMBI IQLIK autoinjector (2.2, 2.6).
- See Full Prescribing Information for preparation and administration instructions. (2.5, 2.6)

3 DOSAGE FORMS AND STRENGTHS

Intravenous Infusion

- Injection: 500 mg/5 mL (100 mg/mL) solution in a single-dose vial (3)
- Injection: 200 mg/2 mL (100 mg/mL) solution in a single-dose vial (3)

Subcutaneous Injection

- Injection: 360 mg/1.8 mL (200 mg/mL) in a single-dose prefilled IQLIK autoinjector (3)

4 CONTRAINDICATIONS

LEQEMBI is contraindicated in patients with serious hypersensitivity to lecanemab-irmb or to any of the excipients of LEQEMBI or LEQEMBI IQLIK. (4)

5 WARNINGS AND PRECAUTIONS

- Amyloid Related Imaging Abnormalities (ARIA): Enhanced clinical vigilance for ARIA is recommended during the first 14 weeks of treatment with LEQEMBI. Risk of ARIA, including symptomatic ARIA, was increased in apolipoprotein E ε4 homozygotes compared to heterozygotes and noncarriers. The risk of ARIA-E and ARIA-H is increased in patients with pretreatment microhemorrhages and/or superficial siderosis. If a patient experiences symptoms suggestive of ARIA, clinical evaluation should be performed, including MRI scanning if indicated. (2.4, 5.1)
- Infusion-Related Reactions: The infusion rate may be reduced, or the infusion may be discontinued, and appropriate therapy administered as clinically indicated. Consider pre-medication at subsequent dosing with antihistamines, non-steroidal anti-inflammatory drugs, or corticosteroids. (5.3)

6 ADVERSE REACTIONS

Most common adverse reactions (at approximately 10% and higher incidence compared to placebo): infusion-related reactions, amyloid related imaging abnormality-microhemorrhages, amyloid related imaging abnormality-edema/effusion, and headache. (6.1)

To report SUSPECTED ADVERSE REACTIONS, contact Eisai Inc. at 1-888-274-2378 or FDA at 1-800-FDA-1088 or www.fda.gov/medwatch.

FULL PRESCRIBING INFORMATION

WARNING: AMYLOID RELATED IMAGING ABNORMALITIES

Monoclonal antibodies directed against aggregated forms of beta amyloid, including LEQEMBI, can cause amyloid related imaging abnormalities (ARIA), characterized as ARIA with edema (ARIA-E) and ARIA with hemosiderin deposition (ARIA-H). Incidence and timing of ARIA vary among treatments. ARIA usually occurs early in treatment and is usually asymptomatic, although serious and life-threatening events can occur. ARIA can be fatal. Serious intracerebral hemorrhages > 1 cm, some of which have been fatal, have been observed in patients treated with this class of medications. Because ARIA-E can cause focal neurologic deficits that can mimic an ischemic stroke, treating clinicians should consider whether such symptoms could be due to ARIA-E before giving thrombolytic therapy to a patient being treated with LEQEMBI [see Warnings and Precautions (5.1), Adverse Reactions (6.1)].

ApoE ε4 Homozygotes

Patients who are apolipoprotein E ε4 (ApoE ε4) homozygotes (approximately 15% of Alzheimer’s disease patients) treated with this class of medications, including LEQEMBI, have a higher incidence of ARIA, including symptomatic, serious, and severe radiographic ARIA, compared to heterozygotes and noncarriers. Testing for ApoE ε4 status should be performed prior to initiation of treatment to inform the risk of developing ARIA. Prior to testing, prescribers should discuss with patients the risk of ARIA across genotypes and the implications of genetic testing results. Prescribers should inform patients that if genotype testing is not performed they can still be treated with LEQEMBI; however, it cannot be determined if they are ApoE ε4 homozygotes and at higher risk for ARIA [see Warnings and Precautions (5.1)].

Consider the benefit of LEQEMBI for the treatment of Alzheimer’s disease and potential risk of serious adverse events associated with ARIA when deciding to initiate treatment with LEQEMBI [see Warnings and Precautions (5.1) and Clinical Studies (14)].

1 INDICATIONS AND USAGE

LEQEMBI is indicated for the treatment of Alzheimer’s disease. Treatment with LEQEMBI should be initiated in patients with mild cognitive impairment or mild dementia stage of disease, the population in which treatment was initiated in clinical trials.

2 DOSAGE AND ADMINISTRATION

2.1 Patient Selection

Confirm the presence of amyloid beta pathology prior to initiating treatment [see Clinical Pharmacology (12.1)].

2.2 Recommended Dosage

Initiate LEQEMBI as an intravenous infusion using the starting dosage (see Table 1). After 18 months, the starting dosage may be continued or a transition to maintenance dosage regimen may be considered, which can be administered by either intravenous infusion or subcutaneous injection (see Table 1). If transitioning from starting dosage to a maintenance dosage regimen, administer the first maintenance dose two weeks after the last starting dose.

Table 1: Starting and Maintenance Dosage Regimens
Route of Administration | Dose | Frequency | Infusion Rate (if Intravenous)
Starting Dosage
Intravenous Only (LEQEMBI) | 10 mg/kg | Once every 2 weeks | Over approximately one hour
Maintenance Dosage
Intravenous (LEQEMBI) | 10 mg/kg | Once every 4 weeks | Over approximately one hour
Subcutaneous (LEQEMBI IQLIK) | 360 mg | Once every week | ------------------------

For intravenous infusion, use LEQEMBI vials. LEQEMBI vials must be diluted before administration [see Dosage and Administration (2.5)].

For subcutaneous administration, use LEQEMBI IQLIK [see Dosage and Administration (2.6)].

2.3 Switching Between Maintenance Dosage Regimens

During maintenance dosage regimen, patients may switch the route of administration (intravenous LEQEMBI or subcutaneous LEQEMBI IQLIK). This transition should be initiated at 1 week following the last maintenance dose of either the intravenous or subcutaneous dosing regimen. Thereafter, follow the dosing schedule for the newly assigned maintenance dosage regimen.

2.4 Monitoring and Dosing Interruption for Amyloid Related Imaging Abnormalities

LEQEMBI can cause amyloid related imaging abnormalities -edema (ARIA-E) and -hemosiderin deposition (ARIA-H) [see Warnings and Precautions (5.1)].

Monitoring for ARIA

Obtain a recent baseline brain magnetic resonance imaging (MRI) prior to initiating treatment with LEQEMBI. Obtain an MRI prior to the 3rd, 5th, 7th, and 14th infusions. In general, the MRI should be performed within approximately one week before the scheduled infusion of LEQEMBI and reviewed prior to proceeding with the infusion. If a patient experiences symptoms suggestive of ARIA, clinical evaluation should be performed, including an MRI if indicated.

Recommendations for Dosing Interruptions in Patients with ARIA

ARIA-E

The recommendations for dosing interruptions for patients with ARIA-E are provided in Table 2.

Table 2: Dosing Recommendations for Patients with ARIA-E
Clinical Symptom Severity^1 | ARIA-E Severity on MRI^2
 | Mild | Moderate | Severe
Asymptomatic | May continue dosing | Suspend dosing^3 | Suspend dosing^3
Mild | May continue dosing based on clinical judgment | Suspend dosing^3
Moderate or Severe | Suspend dosing^3
^1 Clinical Symptom Severity Categories:
Mild: discomfort noticed, but no disruption of normal daily activity.
Moderate: discomfort sufficient to reduce or affect normal daily activity.
Severe: incapacitating, with inability to work or to perform normal daily activity.
^2 See Table 4 for MRI radiographic severity [Warnings and Precautions (5.1)].
^3 Suspend until MRI demonstrates radiographic resolution and symptoms, if present, resolve; consider a follow-up MRI to assess for resolution 2 to 4 months after initial identification. Resumption of dosing should be guided by clinical judgment.

ARIA-H

The recommendations for dosing interruptions for patients with ARIA-H are provided in Table 3.

Table 3: Dosing Recommendations for Patients with ARIA-H
Clinical Symptom Severity |  | ARIA-H Severity on MRI^1
 |  | Mild | Moderate | Severe
Asymptomatic |  | May continue dosing | Suspend dosing^2 | Suspend dosing^3
Symptomatic |  | Suspend dosing^2 | Suspend dosing^2
^1 | See Table 4 for MRI radiographic severity [Warnings and Precautions (5.1)].
^2 | Suspend until MRI demonstrates radiographic stabilization and symptoms, if present, resolve; resumption of dosing should be guided by clinical judgment; consider a follow-up MRI to assess for stabilization 2 to 4 months after initial identification.
^3 | Suspend until MRI demonstrates radiographic stabilization and symptoms, if present, resolve; use clinical judgment in considering whether to continue treatment or permanently discontinue LEQEMBI.

In patients who develop intracerebral hemorrhage greater than 1 cm in diameter during treatment with LEQEMBI, suspend dosing until MRI demonstrates radiographic stabilization and symptoms, if present, resolve. Use clinical judgment in considering whether to continue treatment after radiographic stabilization and resolution of symptoms or permanently discontinue LEQEMBI.

2.5 Preparation and Administration of LEQEMBI for Intravenous Infusion

Dilution

- Prior to intravenous administration, LEQEMBI must be diluted in 250 mL of 0.9% Sodium Chloride Injection, USP.
- Use aseptic technique when preparing the LEQEMBI diluted solution for intravenous infusion.
- Calculate the dose (mg), the total volume (mL) of LEQEMBI solution required, and the number of vials needed based on the patient’s actual body weight and the recommended dose of 10 mg/kg. Each vial contains a LEQEMBI concentration of 100 mg/mL.
- Parenteral drug products should be inspected visually for particulate matter and discoloration prior to administration, whenever solution and container permit. Check that the LEQEMBI solution is clear to opalescent and colorless to pale yellow. Do not use if opaque particles, discoloration, or other foreign particles are present.
- Remove the flip-off cap from the vial. Insert the sterile syringe needle into the vial through the center of the rubber stopper.
- Withdraw the required volume of LEQEMBI from the vial(s) and add to an infusion bag containing 250 mL of 0.9% Sodium Chloride Injection, USP.
- Each vial is for one-time use only. Discard any unused portion.
- Gently invert the infusion bag containing the LEQEMBI diluted solution to mix completely. Do not shake.
- After dilution, immediate use is recommended [see Description (11)]. If not administered immediately, store LEQEMBI refrigerated at 2°C to 8°C (36°F to 46°F) for up to 4 hours, or at room temperature up to 30°C (86°F) for up to 4 hours. Do not freeze.

Administration

• Visually inspect the LEQEMBI diluted solution for particles or discoloration prior to administration. Do not use if it is discolored, opaque, or foreign particles are seen.

• Prior to infusion, allow the LEQEMBI diluted solution to warm to room temperature.

• Infuse the entire volume of the LEQEMBI diluted solution intravenously over approximately one hour through an intravenous line containing a terminal low-protein binding 0.2 micron in-line filter. Flush infusion line to ensure all LEQEMBI is administered.

• Monitor for any signs or symptoms of an infusion-related reaction during the infusion and consider longer periods of observation if clinically indicated. The infusion rate may be reduced, or the infusion may be discontinued, and appropriate therapy administered as clinically indicated. Consider pre-medication at subsequent dosing with antihistamines, non-steroidal anti-inflammatory drugs, or corticosteroids [see Warnings and Precautions (5.3)].

2.6 Preparation and Administration of LEQEMBI IQLIK for Subcutaneous Injection

Instruct patients and/or caregivers on the proper subcutaneous administration of LEQEMBI IQLIK. Direct patients and/or caregivers to follow the directions provided in the Instructions for Use for additional details on administration [see Instructions for Use]. Periodically reassess the ability of the patient or caregiver to safely and adequately administer LEQEMBI IQLIK.

• Before injection, remove LEQEMBI IQLIK from the refrigerator and leave at room temperature for 20 minutes. Do not use an external heat source to heat LEQEMBI IQLIK because heat may damage the product.

• Do not shake LEQEMBI IQLIK.

• Visually inspect LEQEMBI IQLIK for particles or discoloration prior to administration. The solution should be a clear to opalescent, colorless to pale yellow solution, and free of visible particles. Do not use LEQEMBI IQLIK if it is cloudy or there are visible particles.

• Do not use LEQEMBI IQLIK if it looks damaged or has been dropped.

• Sites for injection include the abdomen, upper thigh, and back of the upper arm.

• Do not inject into moles, scars, bruises, tattoos or into areas where the skin is red, hard, tender or injured.

• Monitor for signs or symptoms of an injection reaction.

2.7 Missed Dose

Intravenous Infusion

If a starting dosage or maintenance dosage infusion is missed, administer the next dose as soon as possible.

Subcutaneous Injection

If a scheduled dose of the subcutaneous maintenance dosing regimen is missed, administer LEQEMBI IQLIK as soon as possible up to 6 days after the missed dose and administer the next dose on the regularly scheduled day. Thereafter, resume the original dosing schedule.

3 DOSAGE FORMS AND STRENGTHS

Lecanemab-irmb is a clear to opalescent and colorless to pale yellow solution, available as:

Intravenous Infusion

- Injection: 500 mg/5 mL (100 mg/mL) in a single-dose vial
- Injection: 200 mg/2 mL (100 mg/mL) in a single-dose vial

Subcutaneous Injection

- Injection: 360 mg/1.8 mL (200 mg/mL) in a single-dose prefilled autoinjector

4 CONTRAINDICATIONS

LEQEMBI is contraindicated in patients with serious hypersensitivity to lecanemab-irmb or to any of the excipients of LEQEMBI or LEQEMBI IQLIK. Reactions have included angioedema and anaphylaxis [see Warnings and Precautions (5.2)].

5 WARNINGS AND PRECAUTIONS

5.1 Amyloid Related Imaging Abnormalities

Monoclonal antibodies directed against aggregated forms of beta amyloid, including LEQEMBI, can cause amyloid related imaging abnormalities (ARIA), characterized as ARIA with edema (ARIA-E), which can be observed on MRI as brain edema or sulcal effusions, and ARIA with hemosiderin deposition (ARIA-H), which includes microhemorrhage and superficial siderosis. ARIA can occur spontaneously in patients with Alzheimer’s disease, particularly in patients with MRI findings suggestive of cerebral amyloid angiopathy, such as pretreatment microhemorrhage or superficial siderosis. ARIA-H associated with monoclonal antibodies directed against aggregated forms of beta amyloid generally occurs in association with an occurrence of ARIA-E. ARIA-H of any cause and ARIA-E can occur together.

ARIA usually occurs early in treatment and is usually asymptomatic, although serious and life-threatening events, including seizure and status epilepticus, can occur. ARIA can be fatal. When present, reported symptoms associated with ARIA may include headache, confusion, visual changes, dizziness, nausea, and gait difficulty. Focal neurologic deficits may also occur. Symptoms associated with ARIA usually resolve over time. In addition to ARIA, intracerebral hemorrhages greater than 1 cm in diameter have occurred in patients treated with LEQEMBI.

Consider the benefit of LEQEMBI for the treatment of Alzheimer’s disease and potential risk of serious adverse events associated with ARIA when deciding to initiate treatment with LEQEMBI.

Incidence of ARIA

Symptomatic ARIA occurred in 3% (29/898) of patients treated with LEQEMBI in Study 2 [see Clinical Studies (14)]. Serious symptoms associated with ARIA were reported in 0.7% (6/898) of patients treated with LEQEMBI. Clinical symptoms associated with ARIA resolved in 79% (23/29) of patients during the period of observation. Similar findings were observed in Study 1.

Including asymptomatic radiographic events, ARIA was observed in 21% (191/898) of patients treated with LEQEMBI, compared to 9% (84/897) of patients on placebo in Study 2.

In Study 2, ARIA-E was observed in 13% (113/898) of patients treated with LEQEMBI, compared to 2% (15/897) of patients on placebo. ARIA-H was observed in 17% (152/898) of patients treated with LEQEMBI, compared to 9% (80/897) of patients on placebo. There was no increase in isolated ARIA-H (i.e., ARIA-H in patients who did not also experience ARIA-E) for LEQEMBI compared to placebo.

Incidence of Intracerebral Hemorrhage

Intracerebral hemorrhage greater than 1 cm in diameter was reported in 0.7% (6/898) of patients in Study 2 after treatment with LEQEMBI, compared to 0.1% (1/897) on placebo. Fatal events of intracerebral hemorrhage in patients taking LEQEMBI have been observed.

Risk Factors for ARIA and Intracerebral Hemorrhage

ApoE ε4 Carrier Status

The risk of ARIA, including symptomatic and serious ARIA, is increased in apolipoprotein E ε4 (ApoE ε4) homozygotes.

Approximately 15% of Alzheimer’s disease patients are ApoE ε4 homozygotes. In Study 2, 16% (141/898) of patients in the LEQEMBI arm were ApoE ε4 homozygotes, 53% (479/898) were heterozygotes, and 31% (278/898) were noncarriers. The incidence of ARIA was higher in ApoE ε4 homozygotes (45% on LEQEMBI vs. 22% on placebo) than in heterozygotes (19% on LEQEMBI vs 9% on placebo) and noncarriers (13% on LEQEMBI vs 4% on placebo). Among patients treated with LEQEMBI, symptomatic ARIA-E occurred in 9% of ApoE ε4 homozygotes compared to 2% of heterozygotes and 1% noncarriers. Serious events of ARIA occurred in 3% of ApoE ε4 homozygotes, and approximately 1% of heterozygotes and noncarriers. The recommendations on management of ARIA do not differ between ApoE ε4 carriers and noncarriers [see Dosage and Administration (2.4)]. Testing for ApoE ε4 status should be performed prior to initiation of treatment to inform the risk of developing ARIA. Prior to testing, prescribers should discuss with patients the risk of ARIA across genotypes and the implications of genetic testing results. Prescribers should inform patients that if genotype testing is not performed they can still be treated with LEQEMBI; however, it cannot be determined if they are ApoE ε4 homozygotes and at higher risk for ARIA.

Radiographic Findings of Cerebral Amyloid Angiopathy (CAA)

Neuroimaging findings that may indicate CAA include evidence of prior intracerebral hemorrhage, cerebral microhemorrhage, and cortical superficial siderosis. CAA has an increased risk for intracerebral hemorrhage. The presence of an ApoE ε4 allele is also associated with cerebral amyloid angiopathy.

The baseline presence of at least 2 microhemorrhages or the presence of at least 1 area of superficial siderosis on MRI, which may be suggestive of CAA, have been identified as risk factors for ARIA. Patients were excluded from enrollment in Study 2 for the presence of more than 4 microhemorrhages and additional findings suggestive of cerebral amyloid angiopathy (prior cerebral hemorrhage greater than 1 cm in greatest diameter, superficial siderosis, vasogenic edema) or other lesions (aneurysm, vascular malformation) that could potentially increase the risk of intracerebral hemorrhage.

Concomitant Antithrombotic or Thrombolytic Medication

In Study 2, baseline use of antithrombotic medication (aspirin, other antiplatelets, or anticoagulants) was allowed if the patient was on a stable dose. The majority of exposures to antithrombotic medications were to aspirin. Antithrombotic medications did not increase the risk of ARIA with LEQEMBI. The incidence of intracerebral hemorrhage was 0.9% (3/328 patients) in patients taking LEQEMBI with a concomitant antithrombotic medication at the time of the event, compared to 0.6% (3/545 patients) in those who did not receive an antithrombotic. Patients taking LEQEMBI with an anticoagulant alone or combined with an antiplatelet medication or aspirin had an incidence of intracerebral hemorrhage of 2.5% (2/79 patients), compared to none in patients who received placebo.

Fatal cerebral hemorrhage has occurred in a patient taking an anti-amyloid monoclonal antibody in the setting of focal neurologic symptoms of ARIA and the use of a thrombolytic agent.

Additional caution should be exercised when considering the administration of antithrombotics or a thrombolytic agent (e.g., tissue plasminogen activator) to a patient already being treated with LEQEMBI. Because ARIA-E can cause focal neurologic deficits that can mimic an ischemic stroke, treating clinicians should consider whether such symptoms could be due to ARIA-E before giving thrombolytic therapy in a patient being treated with LEQEMBI.

Caution should be exercised when considering the use of LEQEMBI in patients with factors that indicate an increased risk for intracerebral hemorrhage and in particular for patients who need to be on anticoagulant therapy, or patients with findings on MRI that are suggestive of cerebral amyloid angiopathy.

Radiographic Severity

The radiographic severity of ARIA associated with LEQEMBI was classified by the criteria shown in Table 4.

Table 4: ARIA MRI Classification Criteria
ARIA Type | Radiographic Severity
 | Mild | Moderate | Severe
ARIA-E | FLAIR hyperintensity confined to sulcus and/or cortex/subcortex white matter in one location <5 cm | FLAIR hyperintensity 5 to 10 cm in single greatest dimension, or more than 1 site of involvement, each measuring <10 cm | FLAIR hyperintensity >10 cm with associated gyral swelling and sulcal effacement. One or more separate/ independent sites of involvement may be noted.
ARIA-H microhemorrhage | ≤ 4 new incident microhemorrhages | 5 to 9 new incident microhemorrhages | 10 or more new incident microhemorrhages
ARIA-H superficial siderosis | 1 focal area of superficial siderosis | 2 focal areas of superficial siderosis | > 2 areas of superficial siderosis

In Study 2, the majority of ARIA-E radiographic events occurred early in treatment (within the first 7 doses), although ARIA can occur at any time and patients can have more than 1 episode. The maximum radiographic severity of ARIA-E in patients treated with LEQEMBI was mild in 4% (37/898) of patients, moderate in 7% (66/898) of patients, and severe in 1% (9/898) of patients. Resolution on MRI occurred in 52% of ARIA-E patients by 12 weeks, 81% by 17 weeks, and 100% overall after detection. The maximum radiographic severity of ARIA-H microhemorrhage in patients treated with LEQEMBI was mild in 9% (79/898), moderate in 2% (19/898), and severe in 3% (28/898) of patients; superficial siderosis was mild in 4% (38/898), moderate in 1% (8/898), and severe in 0.4% (4/898). Among patients treated with LEQEMBI, the rate of severe radiographic ARIA-E was highest in ApoE ε4 homozygotes 5% (7/141), compared to heterozygotes 0.4% (2/479) or noncarriers 0% (0/278). Among patients treated with LEQEMBI, the rate of severe radiographic ARIA-H was highest in ApoE ε4 homozygotes 13.5% (19/141), compared to heterozygotes 2.1% (10/479) or noncarriers 1.1% (3/278).

Monitoring and Dose Management Guidelines

Recommendations for dosing in patients with ARIA-E depend on clinical symptoms and radiographic severity [see Dosage and Administration (2.4)]. Recommendations for dosing in patients with ARIA-H depend on the type of ARIA-H and radiographic severity [see Dosage and Administration (2.4)]. Use clinical judgment in considering whether to continue dosing in patients with recurrent ARIA-E.

Baseline brain MRI and periodic monitoring with MRI are recommended [see Dosage and Administration (2.4)]. Enhanced clinical vigilance for ARIA is recommended during the first 14 weeks of treatment with LEQEMBI. If a patient experiences symptoms suggestive of ARIA, clinical evaluation should be performed, including MRI if indicated. If ARIA is observed on MRI, careful clinical evaluation should be performed prior to continuing treatment.

There is no experience in patients who continued dosing through symptomatic ARIA-E, or through asymptomatic but radiographically severe ARIA-E. There is limited experience in patients who continued dosing through asymptomatic but radiographically mild to moderate ARIA-E. There are limited data in dosing patients who experienced recurrent ARIA-E. While experience is limited in these situations, dose management guidelines are provided [see Dosage and Administration (2.4)].

Providers should encourage patients to participate in real world data collection (e.g., registries) to help further the understanding of Alzheimer’s disease and the impact of Alzheimer’s disease treatments. Providers and patients can contact Eisai at 888-274-2378 for a list of currently enrolling programs.

5.2 Hypersensitivity Reactions

Hypersensitivity reactions, including angioedema, bronchospasm, and anaphylaxis, have occurred in patients who were treated with LEQEMBI. If LEQEMBI is being administered intravenously, promptly discontinue the infusion upon the first observation of any signs or symptoms consistent with a hypersensitivity reaction, and initiate appropriate therapy. LEQEMBI is contraindicated in patients with a history of serious hypersensitivity to lecanemab-irmb or to any of the excipients of LEQEMBI or LEQEMBI IQLIK.

5.3 Infusion-Related Reactions

In Study 2, infusion-related reactions were observed in 26% (237/898) of patients treated with LEQEMBI, compared to 7% (66/897) of patients on placebo; and the majority (75%, 178/237) occurred with the first infusion. Infusion-related reactions were mostly mild (69%) or moderate (28%) in severity. Infusion-related reactions resulted in discontinuations in 1% (12/898) of patients treated with LEQEMBI. Symptoms of infusion-related reactions include fever and flu-like symptoms (chills, generalized aches, feeling shaky, and joint pain), nausea, vomiting, hypotension, hypertension, and oxygen desaturation.

After the first infusion in Study 1, 38% of patients treated with LEQEMBI had transient decreased lymphocyte counts to less than 0.9 x10^9/L, compared to 2% in patients on placebo, and 22% of patients treated with LEQEMBI had transient increased neutrophil counts to greater than 7.9 x10^9/L, compared to 1% of patients on placebo. Lymphocyte and neutrophil counts were not obtained after the first infusion in Study 2.

Infusion-related reactions can occur during the infusion or after completion of the infusion. In the event of an infusion-related reaction during the infusion, the infusion rate may be reduced, or the infusion may be discontinued, and appropriate therapy initiated as clinically indicated. Consider prophylactic treatment with antihistamines, acetaminophen, nonsteroidal anti-inflammatory drugs, or corticosteroids prior to future infusions.

6 ADVERSE REACTIONS

The following clinically significant adverse reactions are described elsewhere in the labeling:

- Amyloid Related Imaging Abnormalities [see Warnings and Precautions (5.1)]
- Hypersensitivity Reactions [see Warnings and Precautions (5.2)]
- Infusion-Related Reactions [see Warnings and Precautions (5.3)]

6.1 Clinical Trials Experience

Because clinical trials are conducted under widely varying conditions, adverse reaction rates observed in the clinical trials of a drug cannot be directly compared to rates in the clinical trials of another drug and may not reflect the rates observed in practice.

Clinical Trials with Intravenous Administration

The safety of LEQEMBI has been evaluated in 2090 patients who received at least one dose of LEQEMBI by intravenous infusion. In Studies 1 and 2 in patients with Alzheimer’s disease, 1059 patients received LEQEMBI 10 mg/kg every two weeks by intravenous infusion [see Clinical Studies (14)]. Of these 1059 patients, 50% were female, 79% were White, 15% were Asian, 12% were of Hispanic or Latino ethnicity, and 2% were Black. The mean age at study entry was 72 years (range from 50 to 90 years).

In the combined double-blind, placebo-controlled period and long-term extension period of Studies 1 and 2, 1604 patients received LEQEMBI for at least 6 months, 1261 patients for at least 12 months, and 965 patients for 18 months.

In the double-blind, placebo-controlled period in Study 1, patients stopped study treatment because of an adverse reaction in 15% of patients treated with LEQEMBI, compared to 6% patients on placebo; in Study 2, patients stopped study treatment because of an adverse reaction in 7% of patients treated with LEQEMBI, compared to 3% patients on placebo. In Study 1, the most common adverse reaction leading to discontinuation of LEQEMBI was infusion-related reactions that led to discontinuation in 2% (4/161) of patients treated with LEQEMBI, compared to 1% (2/245) of patients on placebo. In Study 2, the most common adverse reaction leading to discontinuation of LEQEMBI was ARIA-H microhemorrhages that led to discontinuation in 2% (15/898) of patients treated with LEQEMBI, compared to <1% (1/897) of patients on placebo.

Table 5 shows adverse reactions that were reported in at least 5% of patients treated with LEQEMBI and at least 2% more frequently than in patients on placebo in Study 1.

Table 5: Adverse Reactions Reported in at Least 5% of Patients Treated with LEQEMBI 10 mg/kg Every Two Weeks and at least 2% Higher than Placebo in Study 1
Adverse Reaction | LEQEMBI 10 mg/kg Every Two Weeks N=161 % | Placebo N=245 %
Infusion-related reactions | 20 | 3
Headache | 14 | 10
ARIA-E | 10 | 1
Cough | 9 | 5
Diarrhea | 8 | 5

Table 6 shows adverse reactions that were reported in at least 5% of patients treated with LEQEMBI and at least 2% more frequently than in patients on placebo in Study 2.

Table 6: Adverse Reactions Reported in at Least 5% of Patients Treated with LEQEMBI 10 mg/kg Every Two Weeks and at least 2% Higher than Placebo in Study 2
Adverse Reaction | LEQEMBI 10 mg/kg Every Two Weeks N=898 % | Placebo N=897 %
Infusion-related reactions | 26 | 7
ARIA-H | 14 | 8
ARIA-E | 13 | 2
Headache | 11 | 8
Superficial siderosis of central nervous system | 6 | 3
Rash^1 | 6 | 4
Nausea/Vomiting | 6 | 4
^1 Rash includes acne, erythema, infusion site rash, injection site rash, rash, rash erythematous, rash pruritic, skin reactions, and urticaria.

Less Common Adverse Reactions

Atrial fibrillation occurred in 3% of patients treated with LEQEMBI, compared to 2% in patients on placebo. In Study 1, lymphopenia or decreased lymphocyte count was reported in 4% of patients treated with LEQEMBI after the first dose, compared to less than 1% of patients on placebo [see Warnings and Precautions (5.3)]; lymphocytes were not measured after the first dose in Study 2.

Clinical Trials with Subcutaneous Administration

The safety of LEQEMBI IQLIK for maintenance treatment was evaluated in an open-label study, which included 49 patients who received LEQEMBI IQLIK 360 mg by subcutaneous administration once every week. The overall safety profile in these patients was similar to what was observed in patients who received LEQEMBI by intravenous infusion in Study 1 and Study 2. Patients who received LEQEMBI IQLIK experienced localized and systemic injection-related reactions. Localized injection-related reactions included erythema, induration, swelling, heat, pain, pruritis, rash, ecchymosis, and hematoma. Systemic injection-related reactions were observed less frequently, with symptoms of headache, fever, and fatigue. Injection-related reactions in patients receiving LEQEMBI IQLIK were mild or moderate in severity.

8 USE IN SPECIFIC POPULATIONS

8.1 Pregnancy

Risk Summary

There are no adequate data on LEQEMBI use in pregnant women to evaluate for a drug-associated risk of major birth defects, miscarriage, or other adverse maternal or fetal outcomes. No animal studies have been conducted to assess the potential reproductive or developmental toxicity of LEQEMBI.

In the US general population, the estimated background risk of major birth defects and miscarriage in clinically recognized pregnancies is 2% to 4% and 15% to 20%, respectively. The background risk of major birth defects and miscarriage for the indicated population is unknown.

8.2 Lactation

Risk Summary

There are no data on the presence of lecanemab-irmb in human milk, the effects on the breastfed infant, or the effects of the drug on milk production. Published data from other monoclonal antibodies generally indicate low passage of monoclonal antibodies into human milk and limited systemic exposure in the breastfed infant. The effects of this limited exposure are unknown. The developmental and health benefits of breastfeeding should be considered along with the mother’s clinical need for LEQEMBI and any potential adverse effects on the breastfed infant from LEQEMBI or from the underlying maternal condition.

8.4 Pediatric Use

Safety and effectiveness of LEQEMBI in pediatric patients have not been established.

8.5 Geriatric Use

In Studies 1 and 2, the age of patients exposed to LEQEMBI 10 mg/kg every two weeks (n=1059) ranged from 50 to 90 years, with a mean age of 72 years; 81% were 65 years and older, and 39% were 75 years and older. No overall differences in safety or effectiveness of LEQEMBI have been observed between patients 65 years of age and older and younger adult patients.

11 DESCRIPTION

Lecanemab-irmb is a recombinant humanized immunoglobulin gamma 1 (IgG1) monoclonal antibody directed against aggregated soluble and insoluble forms of amyloid beta, and is expressed in a Chinese hamster ovary cell line. Lecanemab-irmb has an approximate molecular weight of 150 kDa.

LEQEMBI Injection for Intravenous Use

LEQEMBI (lecanemab-irmb) injection is a sterile, preservative-free, clear to opalescent and colorless to pale yellow solution for intravenous infusion after dilution. LEQEMBI is supplied in single-dose vials available in concentrations of 500 mg/5 mL (100 mg/mL) or 200 mg/2 mL (100 mg/mL).

Each mL of solution contains 100 mg of lecanemab-irmb and arginine hydrochloride (42.13 mg), histidine (0.18 mg), histidine hydrochloride monohydrate (4.99 mg), polysorbate 80 (0.50 mg), and Water for Injection at an approximate pH of 5.0.

LEQEMBI IQLIK Injection for Subcutaneous Use

LEQEMBI IQLIK (lecanemab-irmb) injection is a sterile, preservative-free, clear to opalescent and colorless to pale yellow solution for subcutaneous use. LEQEMBI IQLIK is supplied in a single-dose prefilled autoinjector available in the concentration of 360 mg/1.8 mL with a 29-gauge fixed ½-inch needle. Each LEQEMBI IQLIK autoinjector contains 360 mg/1.8 mL lecanemab-irmb formulated in: arginine hydrochloride (75.83 mg), histidine (0.25 mg), histidine hydrochloride monohydrate (9.09 mg), polysorbate 80 (0.90 mg), and Water for Injection, USP.

12 CLINICAL PHARMACOLOGY

12.1 Mechanism of Action

Lecanemab-irmb is a humanized immunoglobulin gamma 1 (IgG1) monoclonal antibody directed against aggregated soluble and insoluble forms of amyloid beta. The accumulation of amyloid beta plaques in the brain is a defining pathophysiological feature of Alzheimer’s disease. LEQEMBI reduces amyloid beta plaques, as evaluated in Study 1 and Study 2 [see Clinical Studies (14)].

12.2 Pharmacodynamics

Effect of LEQEMBI on Amyloid Beta Pathology

The effect of LEQEMBI on amyloid beta plaque levels in the brain was evaluated using Positron Emission Tomography (PET) imaging. The PET signal was quantified using both the standard uptake value ratio (SUVR) and Centiloid scale to estimate levels of amyloid beta plaque in composites of brain areas expected to be widely affected by Alzheimer’s disease pathology (frontal, parietal, lateral temporal, sensorimotor, and anterior and posterior cingulate cortices), compared to a brain region expected to be spared of such pathology (cerebellum).

LEQEMBI reduced amyloid beta plaque in a dose- and time-dependent manner in the dose-ranging study (Study 1) and in a time-dependent manner in single-dosing regimen study (Study 2) compared to placebo [see Clinical Studies (14)].

In Study 1, treatment with LEQEMBI 10 mg/kg every two weeks reduced amyloid beta plaque levels in the brain, producing reductions in PET SUVR compared to placebo at both Weeks 53 and 79 (P<0.0001). The magnitude of the reduction was time- and dose-dependent.

During an off-treatment period in Study 1 (range from 9 to 59 months; mean of 24 months), SUVR and Centiloid values began to increase with a mean rate of increase of 2.6 Centiloids/year, however, treatment difference relative to placebo at the end of the double-blind, placebo-controlled period in Study 1 was maintained.

In Study 2, treatment with LEQEMBI 10 mg/kg every two weeks reduced amyloid beta plaque levels in the brain, producing reductions compared to placebo starting at Week 13 and continuing through Week 79 (P<0.0001). After Week 79 of treatment with LEQEMBI 10 mg/kg every two weeks, 67% of patients had amyloid levels less than 30 Centiloids as measured by PET. Reduction of amyloid to levels less than 30 Centiloids was inversely related to amyloid PET levels at baseline. The percentage of patients achieving amyloid levels less than 30 Centiloids after continuous treatment with LEQEMBI 10 mg/kg every two weeks is predicted to increase over time. It is predicted that, after Week 79 of treatment with LEQEMBI intravenous infusion of 10 mg/kg every 2 weeks, transitioning to a dosing regimen of either LEQEMBI intravenous infusion of 10 mg/kg every 4 weeks or a LEQEMBI IQLIK subcutaneous injection of 360 mg once a week will also continue the reduction in amyloid beta plaque levels. Based on exposure-response modeling, the intravenous (10 mg/kg every 4 weeks) and subcutaneous (360 mg once weekly) maintenance dosing regimens of lecanemab-irmb are predicted to have similar reduction of amyloid beta plaque levels.

An increase in plasma Aβ42/40 ratio (Table 6) and CSF Aβ[1-42] was observed with LEQEMBI 10 mg/kg every two weeks dosing compared to placebo. Exposure-response modeling predicts that, after Week 79 of treatment with LEQEMBI intravenous infusion of 10 mg/kg every 2 weeks, transitioning to a dosing regimen of either LEQEMBI intravenous infusion of 10 mg/kg every 4 weeks or a LEQEMBI IQLIK subcutaneous injection of 360 mg once a week will maintain increases in the plasma Aβ42/40 ratio.

Effect of LEQEMBI on Tau Pathophysiology

A reduction in plasma p-tau181 (Table7), CSF p-tau181, and CSF t-tau was observed with LEQEMBI 10 mg/kg every two weeks compared to placebo. Exposure-response modeling predicts that, after Week 79 of treatment with LEQEMBI intravenous infusion of 10 mg/kg every two weeks, transitioning to a dosing regimen of LEQEMBI intravenous infusion of 10 mg/kg every 4 weeks or a LEQEMBI IQLIK subcutaneous injection of 360 mg once a week will maintain the reduction in plasma p-tau181.

Table7: Effect of LEQEMBI on Plasma Aβ42/40 and Plasma p-tau181 in Study 1 and Study 2
Biomarker Endpoints | Study 1 |  | Study 2
 | LEQEMBI 10 mg/kg Every Two Weeks | Placebo | LEQEMBI 10 mg/kg Every Two Weeks | Placebo
Plasma Aβ42/40^2 | N=43 | N=88 | N=797 | N=805
Mean baseline | 0.08 | 0.09 | 0.09 | 0.09
Adjusted mean change from baseline at Month 18^3 | 0.01 | <0.01 | 0.01 | <0.01
Difference from placebo | 0.01 (P=0.0036) ^1 |  | 0.01 (P<0.0001) ^1
Plasma p-tau181 (pg/mL)^2 | N=84 | N=179 | N=746 | N=752
Mean baseline | 4.65 | 4.44 | 3.70 | 3.74
Adjusted mean change from baseline at Month 18^3 | -1.11 | 0.08 | -0.58 | 0.20
Difference from placebo | -1.20 (P<0.0001) ^1 |  | -0.78 (P<0.0001) ^1
N is the number of patients with baseline value.
^1 P values were not statistically controlled for multiple comparisons.
^2 Results should be interpreted with caution due to uncertainties in bioanalysis.
^3 Month 18 represents Week 79 in Study 1 and Week 77 in Study 2.

A substudy was conducted in Study 2 to evaluate the effect of LEQEMBI on neurofibrillary tangles composed of tau protein using PET imaging (^18F-MK6240 tracer). The PET signal was quantified using the SUVR method to estimate brain levels of tau in brain regions expected to be affected by Alzheimer’s disease pathology (whole cortical gray matter, meta-temporal, frontal, cingulate, parietal, occipital, medial temporal, and temporal) in the study population, compared to a brain region expected to be spared of such pathology (cerebellum). The adjusted mean change from baseline in tau PET SUVR, relative to placebo, was in favor of LEQEMBI in the medial temporal (P<0.01), meta temporal (P<0.05), and temporal (P<0.05) regions. No statistically significant differences were observed for the whole cortical gray matter, frontal, cingulate, parietal, or occipital regions.

Exposure-Response Relationships

Model-based exposure-response analyses demonstrated that higher exposures to lecanemab-irmb were associated with greater reduction in clinical decline on Clinical Dementia Rating scale Sum of Boxes (CDR-SB) and Alzheimer Disease Assessment Scale – Cognitive Subscale 14 (ADAS-Cog14). In addition, higher exposures to lecanemab-irmb were associated with greater reduction in amyloid beta plaque. An association between reduction in amyloid beta plaque and clinical decline on CDR-SB and ADAS-Cog14 was also observed.

Higher exposures to lecanemab-irmb were also associated with greater increase in plasma Aβ42/40 ratio and greater reduction in plasma p-tau181.

12.3 Pharmacokinetics

Steady-state concentrations of lecanemab-irmb were reached after 6 weeks of 10 mg/kg administered every 2 weeks and systemic accumulation was 1.4-fold. The peak concentration (Cmax) and area under the plasma concentration versus time curve (AUC) of lecanemab-irmb increased dose proportionally in the dose range of 0.3 to 15 mg/kg following single dose.

The estimated mean steady-state concentrations of lecanemab-irmb following 10 mg/kg biweekly intravenous infusion, 10 mg/kg monthly intravenous infusion and 360 mg weekly subcutaneous administration by autoinjector are provided in Table 8. Using population pharmacokinetic modeling and simulation, the intravenous (10 mg/kg once every 4 weeks) and subcutaneous (360 mg once weekly) maintenance dosing regimens of lecanemab-irmb were predicted to have similar pharmacokinetic exposure.

Table 8: Estimated Systemic Exposure of Lecanemab-irmb at Steady State in Patients with Alzheimer’s Disease*
 | Cavg,ss (mcg/mL) Mean (CV%)
Intravenous infusion 10 mg/kg every two weeks | 156 (37.7)
Intravenous infusion 10 mg/kg every four weeks | 78.1 (37.7)
Subcutaneous injection 360 mg weekly | 83.1 (58.8)
*Based on simulations in 1000 virtual patients

Absorption

The bioavailability of lecanemab-irmb following subcutaneous administration of 360 mg by autoinjector relative to a 10 mg/kg intravenous infusion in patients was approximately 53% and was not affected by the injection site (abdomen, upper thigh, or back of the upper arm).

Distribution

The mean value (95% CI) for central volume of distribution at steady state is 3.24 (3.18-3.30) L.

Elimination

Lecanemab-irmb is degraded by proteolytic enzymes in the same manner as endogenous IgGs. The clearance of lecanemab-irmb (95% CI) is 0.370 (0.353-0.384) L/day. The terminal half-life is 5 to 7 days.

Specific Populations

Sex, body weight, and albumin were found to impact exposure to lecanemab-irmb. However, none of these covariates were found to be clinically significant.

Patients with Renal or Hepatic Impairment

No clinical studies were conducted to evaluate the pharmacokinetics of lecanemab-irmb in patients with renal or hepatic impairment. Lecanemab-irmb is degraded by proteolytic enzymes and is not expected to undergo renal elimination or metabolism by hepatic enzymes.

12.6 Immunogenicity

The observed incidence of anti-drug antibodies (ADA) is highly dependent on the sensitivity and specificity of the assay. Differences in assay methods preclude meaningful comparisons of the incidence of ADA in the studies described below with the incidence of ADA in other studies, including those of lecanemab-irmb or of other lecanemab products.

Intravenous Infusion

During the 18-month treatment period in Study 2, 3.4% (30/883) of patients treated with LEQEMBI 10 mg/kg every two weeks developed treatment-emergent anti-lecanemab-irmb antibodies, and 1.9% (17/885) developed neutralizing antibodies. Among LEQEMBI-treated patients who developed anti-lecanemab-irmb antibodies, mean trough concentrations of lecanemab-irmb were lower at various time points compared to patients who had not developed anti-lecanemab-irmb antibodies. Although there was no clear clinically meaningful impact of ADA (including neutralizing antibodies) on the pharmacodynamics, safety, or efficacy in any patient receiving LEQEMBI over the treatment duration of 18 months, given the low incidence of ADA, the available data are too limited to conclusively assess the impact of ADAs on the safety and efficacy of LEQEMBI.

Subcutaneous Injection

After 18 months of intravenous LEQEMBI 10 mg/kg once every 2 weeks, patients who received 360 mg subcutaneous LEQEMBI IQLIK once weekly in the open-label portion of Study 2 were assessed for immunogenicity using a different assay that was drug-tolerant for anti-lecanemab-irmb antibodies and neutralizing antibodies. The anti-lecanemab-irmb antibody incidence was 2.0% (1/49) following a median treatment duration of 83 days with 360 mg subcutaneous LEQEMBI IQLIK. Neutralizing anti-lecanemab-irmb antibodies were not detected in this patient. Because of the limited data regarding anti-lecanemab-irmb antibodies, there is insufficient information to characterize the effects of anti-lecanemab-irmb antibodies on the pharmacokinetics, pharmacodynamics, safety, or effectiveness of subcutaneous LEQEMBI IQLIK.

13 NONCLINICAL TOXICOLOGY

13.1 Carcinogenesis, Mutagenesis, Impairment of Fertility

Carcinogenesis

Carcinogenicity studies have not been conducted.

Mutagenesis

Genotoxicity studies have not been conducted.

Impairment of Fertility

No studies in animals have been conducted to assess the effects of lecanemab-irmb on male or female fertility. No adverse effects on male or female reproductive organs were observed in a 39-week intravenous toxicity study in monkeys administered lecanemab-irmb weekly at doses up to 100 mg/kg. The highest dose tested was associated with plasma exposures (Cave) approximately 27 times that in humans at the recommended human dose (10 mg/kg every two weeks).

14 CLINICAL STUDIES

The efficacy of LEQEMBI was evaluated in two double-blind, placebo-controlled, parallel-group, randomized studies (Study 1, NCT01767311; Study 2 NCT03887455) in patients with Alzheimer’s disease (patients with confirmed presence of amyloid pathology and mild cognitive impairment [64% of patients in Study 1; 62% of patients in Study 2] or mild dementia stage of disease [36% of patients in Study 1; 38% of patients in Study 2], consistent with Stage 3 and Stage 4 Alzheimer’s disease). In both studies, patients were enrolled with a Clinical Dementia Rating (CDR) global score of 0.5 or 1.0 and a Memory Box score of 0.5 or greater. All patients had a Mini-Mental State Examination (MMSE) score of ≥22 and ≤30, and had objective impairment in episodic memory as indicated by at least 1 standard deviation below age-adjusted mean in the Wechsler-Memory Scale-IV Logical Memory II (subscale) (WMS-IV LMII). Patients were enrolled with or without concomitant approved therapies (cholinesterase inhibitors and the N-methyl-D-aspartate antagonist memantine) for Alzheimer’s disease. The dosage of 10 mg/kg administered once every 2 weeks by intravenous infusion was assessed in the 18-month placebo-controlled portions of Study 1 and Study 2 and continued in the optional long-term extension in each study. Transitioning to intravenous 10 mg/kg once every 4 weeks or subcutaneous 360 mg every week after 18 months of dosing is supported by pharmacokinetic and pharmacodynamic modeling using observed data [see Clinical Pharmacology (12.2)]; however, there are limited data to assess the long-term clinical benefit of transitioning to the dosing regimen of intravenous 10 mg/kg once every 4 weeks or subcutaneous 360 mg every week [see Dosage and Administration (2.2)].

Study 1

In Study 1, 856 patients were randomized to receive one of 5 doses (161 of which were randomized to the recommended dosing regimen of 10 mg/kg every two weeks) of intravenous infusion of LEQEMBI or placebo (n=247). Of the total number of patients randomized, 71.4% were ApoE ε4 carriers and 28.6% were ApoE ε4 non-carriers. During the study, the protocol was amended to no longer randomize ApoE ε4 carriers to the 10 mg/kg every two weeks dose arm. ApoE ε4 carriers who had been receiving LEQEMBI 10 mg/kg every two weeks for 6 months or less were discontinued from study drug. As a result, in the LEQEMBI 10 mg/kg every two weeks arm, 30.3% of patients were ApoE ε4 carriers and 69.7% were ApoE ε4 non-carriers. At baseline, the mean age of randomized patients was 71 years, with a range of 50 to 90 years. Fifty percent of patients were male and 90% were White.

In Study 1, a subgroup of 315 patients were enrolled in the amyloid PET substudy; of these, 277 were evaluated at Week 79. Results from the amyloid beta PET substudy are described in Figure 1 and Table 9. Plasma biomarkers are described in Table 7.

Figure 1: Reduction in Brain Amyloid Beta Plaque (Adjusted Mean Change from Baseline in Amyloid Beta PET Composite, SUVR and Centiloids) in Study 1

Table 9: Results for Amyloid Beta PET in Study 1
Biomarker Endpoints | LEQEMBI 10 mg/kg Every Two Weeks | Placebo
Amyloid Beta PET Composite SUVR | N=44 | N=98
Mean baseline | 1.373 | 1.402
Adjusted mean change from baseline at Week 79 Difference from placebo | -0.306 -0.310 (P<0.001) ^1 | 0.004
Amyloid Beta PET Centiloid | N=44 | N=98
Mean baseline | 78.0 | 84.8
Adjusted mean change from baseline at Week 79 Difference from placebo | -72.5 -73.5 (P<0.001) ^1 | 1.0
N is the number of patients with baseline value.
^1 P values were not statistically controlled for multiple comparisons.

The primary endpoint was change from baseline on a weighted composite score consisting of selected items from the Clinical Dementia Rating scale Sum of Boxes (CDR-SB), MMSE, and Alzheimer Disease Assessment Scale – Cognitive Subscale 14 (ADAS-Cog14) at Week 53. LEQEMBI had a 64% likelihood of 25% or greater slowing of progression on the primary endpoint relative to placebo at Week 53, which did not meet the prespecified success criterion of 80%.

Key secondary efficacy endpoints included the change from baseline in amyloid PET SUVR composite at Week 79 and change from baseline in the CDR-SB and ADAS-Cog14 at Week 79. Results for clinical assessments showed less change from baseline in CDR-SB and ADAS-Cog14 scores at Week 79 in the LEQEMBI group than in patients on placebo (CDR-SB: -0.40 [26%], 90% CI [-0.82, 0.03]; ADAS-Cog14: -2.31 [47%], 90% CI [-3.91, -0.72]).

After the 79-week double-blind, placebo-controlled period of Study 1, patients could enroll in an open-label extension period for up to 260 weeks, which was initiated after a gap period (range 9 to 59 months; mean 24 months) off treatment.

Study 2

In Study 2, 1795 patients were enrolled and randomized 1:1 to receive intravenous infusion of LEQEMBI 10 mg/kg or placebo once every 2 weeks. Of the total number of patients randomized, 69% were ApoE ε4 carriers and 31% were ApoE ε4 non-carriers. Overall median age of patients was 72 years, with a range of 50 to 90 years. Fifty-two percent were women, and 1381 (77%) were White, 303 (17%) were Asian, and 47 (3%) were Black.

The randomization was stratified according to clinical subgroup (mild cognitive impairment or mild dementia stage of the disease); the presence or absence of concomitant approved therapies for Alzheimer’s disease at baseline (cholinesterase inhibitors and the N-methyl-D-aspartate antagonist memantine); ApoE ε4 carrier status; and geographical region.

The primary efficacy outcome was change from baseline at 18 months in the CDR-SB. Key secondary endpoints included change from baseline at 18 months for the following measures: amyloid Positron Emission Tomography (PET) using Centiloids, ADAS-Cog14, and Alzheimer's Disease Cooperative Study-Activities of Daily Living Scale for Mild Cognitive Impairment (ADCS MCI-ADL).

LEQEMBI treatment met the primary endpoint and reduced clinical decline on the global cognitive and functional scale, CDR-SB, compared to placebo at 18 months (-0.45 [-27%], P<0.0001).

Statistically significant differences (P<0.01) between treatment groups were also seen in the results for ADAS-Cog14 and ADCS MCI-ADL at 18 months, as presented in Table 10.

Both ApoE ε4 carriers and ApoE ε4 noncarriers showed statistically significant treatment differences for the primary endpoint and all secondary endpoints. In an exploratory subgroup analysis of ApoE ε4 homozygotes, which represented 15% of the trial population, a treatment effect was not observed with LEQEMBI treatment on the primary endpoint, CDR-SB, compared to placebo, although treatment effects that favored LEQEMBI were observed for the secondary clinical endpoints, ADAS-Cog14 and ADCS MCI-ADL. Treatment effects on disease-relevant biomarkers (amyloid beta PET, plasma Aβ42/40 ratio, plasma p-tau 181) also favored LEQEMBI in the ApoE ε4 homozygous subgroup.

Starting at six months, across all time points, LEQEMBI treatment showed statistically significant changes in the primary and all key secondary endpoints from baseline compared to placebo; see Figure 2.

Table 10: Results for CDR-SB, ADAS-Cog14, and ADCS MCI-ADL in Study 2
Clinical Endpoints | LEQEMBI 10 mg/kg Every Two Weeks | Placebo
CDR-SB | N=859 | N=875
Mean baseline | 3.17 | 3.22
Adjusted mean change from baseline at 18 months (%) Difference from placebo | 1.21 -0.45 (-27%) (P<0.0001) | 1.66
ADAS-Cog14 | N=854 | N=872
Mean baseline | 24.45 | 24.37
Adjusted mean change from baseline at 18 months (%) Difference from placebo | 4.14 -1.44 (-26%) (P=0.0007) | 5.58
ADCS MCI-ADL | N=783 | N=796
Mean baseline | 41.2 | 40.9
Adjusted mean change from baseline at 18 months Difference from placebo | -3.5 (-37%) 2.0 (P<0.0001) | -5.5

Figure 2: Adjusted Mean Change from Baseline in CDR-SB in Study 2

16 HOW SUPPLIED/STORAGE AND HANDLING

16.1 How Supplied

LEQEMBI single-dose vials and LEQEMBI IQLIK single-dose prefilled autoinjectors contain lecanemab-irmb as a sterile, preservative-free, clear to opalescent, and colorless to pale yellow solution, available as described below.

Intravenous Infusion

Each LEQEMBI glass vial is closed with a stopper and flip cap and is available as follows:

Strength | Pack Size | NDC
Injection: 500 mg/5 mL (100 mg/mL) | Carton of 1 single-dose vial | 62856-215-01
Injection: 200 mg/2 mL (100 mg/mL) | Carton of 1 single-dose vial | 62856-212-01

Subcutaneous Injection

Each LEQEMBI IQLIK prefilled autoinjector consists of a 2.25 mL glass syringe with a fixed 29-gauge ½-inch needle with needle guard and is available as follows:

Strength | Pack Size | NDC
Injection: 360 mg/1.8 mL (200 mg/mL) | Carton of 1 single-dose prefilled autoinjector | 62856-220-01

LEQEMBI IQLIK is not made with natural rubber latex.

16.2 Storage and Handling

Intravenous Infusion

Unopened Vial

- Store LEQEMBI vials in a refrigerator at 2°C to 8°C (36°F to 46°F).
- Store in the original carton to protect from light.
- Do not freeze or shake.

Diluted Solution

For storage of the diluted infusion solution, see Dosage and Administration (2.5).

Subcutaneous Injection

- Store LEQEMBI IQLIK autoinjectors in a refrigerator at 2°C to 8°C (36°F to 46°F).
- Store in original carton to protect from light.
- Do not freeze.
- If needed, the autoinjector can be stored at room temperature up to 25°C (77°F) in the original carton for up to 14 days. Once the autoinjector has been stored at room temperature, do not return it to the refrigerator.
- Discard the autoinjector if these conditions are exceeded.

17 PATIENT COUNSELING INFORMATION

Advise the patient and/or caregiver to read the FDA-approved patient labeling (Medication Guide and Instructions for Use).

Amyloid Related Imaging Abnormalities

Inform patients that LEQEMBI may cause Amyloid Related Imaging Abnormalities or “ARIA”. ARIA most commonly presents as a temporary swelling in areas of the brain that usually resolves over time. Some people may also have small spots of bleeding in or on the surface of the brain. Inform patients that most people with swelling in areas of the brain do not experience symptoms; however, some people may experience symptoms such as headache, confusion, dizziness, vision changes, nausea, aphasia, weakness, or seizure. Instruct patients to notify their healthcare provider immediately if these symptoms occur. Clinical evaluation should be performed, and an MRI may be considered. Inform patients that serious symptoms of ARIA may occur and that ARIA can be fatal. Inform patients that events of intracerebral hemorrhage greater than 1 cm in diameter have been reported infrequently in patients taking LEQEMBI, and that the use of antithrombotic or thrombolytic medications while taking LEQEMBI may increase the risk of bleeding in the brain. Notify patients that their healthcare provider will perform MRI scans to monitor for ARIA [see Warnings and Precautions (5.1)].

Inform patients that although ARIA can occur in any patient treated with LEQEMBI, there is an increased risk in patients who are ApoE ε4 homozygotes and that testing for ApoE ε4 status should be performed prior to initiation of treatment to inform the risk of developing ARIA. Prior to testing, discuss with patients the risk of ARIA across genotypes and the implications of genetic testing results. Inform patients that if testing is not performed, it cannot be determined if they are ApoE ε4 homozygotes and at a higher risk for ARIA.

Inform patients that some symptoms of ARIA-E can mimic ischemic stroke and that their healthcare providers may need to perform additional testing to determine how to treat those symptoms in patients taking LEQEMBI. Advise patients to carry information that they are being treated with LEQEMBI.

Patient Registry

Providers should encourage patients to participate in real world data collection (e.g., registries) to help further the understanding of Alzheimer’s disease and the impact of Alzheimer’s disease treatments. Providers and patients can contact Eisai at 888-274-2378 for a list of currently enrolling programs [see Warnings and Precautions (5.1)].

Hypersensitivity Reactions

Inform patients that hypersensitivity reactions, including angioedema and anaphylaxis have occurred in patients who were treated with LEQEMBI. Advise patients to seek immediate medical attention if they experience any symptoms of serious or severe hypersensitivity reactions [see Warnings and Precautions (5.2)].

Infusion-Related Reactions

For patients receiving LEQEMBI via intravenous infusion, advise them of the potential risk of infusion-related reactions, which can include flu-like symptoms, nausea, vomiting, and changes in blood pressure. Advise patients that most infusion-related reactions occur with the first infusion but may occur with any of the infusions during treatment. Advise patients that symptoms can occur during infusion or after they leave the infusion center and to contact their healthcare provider if infusion-related reactions occur [see Warnings and Precautions (5.3)].

Injection-Related Reactions

For patients receiving LEQEMBI IQLIK via subcutaneous injection, advise them of the potential risks of injection reactions, which may present as erythema, induration, swelling, heat, rash, pain, itching, ecchymosis and hematoma at the injection site, but may also present with symptoms such as headache, fever and fatigue. Instruct patients to contact their healthcare provider if injection-related reactions occur [see Adverse Reactions (6.1)].

Manufactured by
Eisai Inc.
Nutley, NJ 07110
U.S. License No. 1862

LEQEMBI® is a registered trademark of Eisai R&D Management Co., Ltd.
LEQEMBI IQLIK™ is a trademark of Eisai R&D Management Co., Ltd.

© 2025 Eisai Inc. and Biogen

MEDICATION GUIDE
LEQEMBI® (leh-kem’-bee)
(lecanemab-irmb)
injection, for intravenous or subcutaneous use

What is the most important information I should know about LEQEMBI?
LEQEMBI can cause serious side effects including:

- Amyloid Related Imaging Abnormalities or “ARIA”. ARIA is a side effect that does not usually cause any symptoms but serious symptoms can occur. ARIA can be fatal. It is most commonly seen as temporary swelling in areas of the brain that usually resolves over time. Some people may also have small spots of bleeding in or on the surface of the brain, and infrequently, larger areas of bleeding in the brain can occur. Most people who develop ARIA do not get symptoms; however, some people may have symptoms, such as:

○ headache

○ vision changes

○ seizures

○ confusion

○ nausea

○ difficulty speaking

○ dizziness

○ difficulty walking

○ muscle weakness

Some people have a genetic risk factor (homozygous apolipoprotein E gene carriers) that may cause an increased risk for ARIA. Talk to your healthcare provider about testing to see if you have this risk factor.
You may be at a higher risk of developing bleeding in the brain if you take medicines to reduce blood clots from forming (antithrombotic medicines) while receiving LEQEMBI.
Your healthcare provider will do magnetic resonance imaging (MRI) scans before and during your treatment with LEQEMBI to check you for ARIA.
You should carry information that you are receiving LEQEMBI which can cause ARIA and that ARIA symptoms can look like stroke symptoms.
Call your healthcare provider or go to the nearest hospital emergency room right away if you have any of the symptoms listed above.
There are registries that collect information on treatments for Alzheimer’s disease. Your healthcare provider can help you become enrolled in these registries. For more information, call Eisai at 888-274-2378.

What is LEQEMBI?
LEQEMBI is a prescription medicine used to treat people with Alzheimer’s disease.
It is not known if LEQEMBI is safe and effective in children.

Do not receive LEQEMBI if you:

- have serious allergic reactions to lecanemab-irmb or to any of the ingredients in LEQEMBI or LEQEMBI IQLIK. See the end of this Medication Guide for a complete list of ingredients in LEQEMBI or LEQEMBI IQLIK.

Before receiving LEQEMBI, tell your healthcare provider about all of your medical conditions, including if you:

- are pregnant or plan to become pregnant. It is not known if LEQEMBI will harm your unborn baby. Tell your healthcare provider if you become pregnant during your treatment with LEQEMBI.
- are breastfeeding or plan to breastfeed. It is not known if lecanemab-irmb (the active ingredient in LEQEMBI) passes into your breast milk. Talk to your healthcare provider about the best way to feed your baby while receiving LEQEMBI.

Tell your healthcare provider about all of the medicines you take, including prescription and over-the-counter medicines, vitamins, and herbal supplements.
Especially tell your healthcare provider if you take medicines to reduce blood clots from forming (antithrombotic medicines, including aspirin). Ask your healthcare provider for a list of these medicines if you are not sure.
Know the medicines you take. Keep a list of them to show your healthcare provider and pharmacist when you get a new medicine.

How will I receive LEQEMBI?
When given in a vein (intravenously)

- LEQEMBI is given by a healthcare provider through a needle placed in your vein (intravenous (IV) infusion) in your arm.
- Your healthcare provider will tell you how often you should receive LEQEMBI. Each infusion will last about 1 hour.
- If you miss an infusion of LEQEMBI, you should receive your next dose as soon as possible.

When given under the skin (subcutaneously)
Read the detailed Instructions for Use that comes with your LEQEMBI IQLIK for information about the right way to prepare and give your LEQEMBI IQLIK injections at home.

- Your healthcare provider will show you how to use LEQEMBI IQLIK and tell you how often you should use it. Use LEQEMBI IQLIK exactly as your healthcare provider tells you to.
- LEQEMBI IQLIK is given as an injection under your skin (subcutaneous injection), into the front of your thighs or stomach-area (abdomen) by you or a caregiver. A caregiver may also give you an injection of LEQEMBI IQLIK in the back of your upper arm.
- Do not inject into moles, scars, bruises, tattoos, or into areas where the skin is red, hard, tender, or injured.
- Use a different injection site the next time you use LEQEMBI IQLIK.
- If you miss a dose of LEQEMBI IQLIK, inject the missed dose as soon as possible up to 6 days after the missed dose. Continue (resume) your next injection on your regular dosing schedule.

What are the possible side effects of LEQEMBI?
LEQEMBI can cause serious side effects, including:

- see “What is the most important information I should know about LEQEMBI?”
- serious allergic reactions. Swelling of the face, lips, mouth, or tongue, hives, or difficulty breathing have happened during treatment with LEQEMBI. Tell your healthcare provider if you have any symptoms of a serious allergic reaction during or after LEQEMBI infusion.
- infusion-related reactions. Infusion-related reactions are a common side effect with LEQEMBI injection into a vein (intravenously), which can be serious. You will receive your infusion at a healthcare facility. If a serious infusion reaction happens while you are receiving LEQEMBI, your infusion may be stopped. Serious infusion reactions can also occur after completion of the infusion. Tell your healthcare provider right away if you get these symptoms during an infusion or after completion of the LEQEMBI infusion:

○ fever

○ dizziness or lightheadedness

○ flu-like symptoms (chills, body aches, feeling shaky, and joint pain)

○ changes in your heart rate or feel like your chest is pounding

○ nausea

○ difficulty breathing or shortness of breath

○ vomiting

○ changes in blood pressure

If you have an infusion-related reaction, your healthcare provider may give you medicines before your LEQEMBI infusions to decrease your chance of having an infusion-related reaction. These medicines may include antihistamines, anti-inflammatory medicines, or steroids.

- injection-related reactions. Injection-related reactions may occur with LEQEMBI injection under the skin (subcutaneous injection with LEQEMBI IQLIK). Redness, swelling, heat, pain, itching, rash, bruising and blood collection under the skin at the injection site may be observed. Headache, fatigue, or fever may also be observed after an injection. Tell your healthcare provider if you experience these symptoms during or after an injection.

The most common side effects of LEQEMBI include:

- infusion-related reactions
- swelling in areas of the brain, with or without small spots of bleeding in or on the surface of the brain (ARIA)
- headache

These are not all the possible side effects of LEQEMBI. For more information, ask your healthcare provider or pharmacist.
Call your doctor for medical advice about side effects. You may report side effects to FDA at 1-800-FDA-1088.

How should I store LEQEMBI IQLIK?

- Store LEQEMBI IQLIK autoinjectors in a refrigerator between 36°F to 46°F (2°C to 8°C).
- Do not freeze.
- Keep LEQEMBI IQLIK autoinjector in the original package until ready to use, to protect from light.
- LEQEMBI IQLIK may be stored at room temperature up to 77°F (25°C) for up to 14 days in the original package. Do not place it back in the refrigerator if it has been brought to room temperature.
- Do not shake LEQEMBI IQLIK.
- Throw away (dispose of) LEQEMBI IQLIK that is out of date, or if it is not stored the right way.

Keep LEQEMBI IQLIK and all medicines out of the reach of children.

General information about the safe and effective use of LEQEMBI.
Medicines are sometimes prescribed for purposes other than those listed in a Medication Guide. Do not use LEQEMBI for a condition for which it was not prescribed. Do not give LEQEMBI to other people, even if they have the same symptoms that you have. It may harm them.
You can ask your pharmacist or healthcare provider for information about LEQEMBI that is written for health professionals.

What are the ingredients in LEQEMBI?
Active ingredient: lecanemab-irmb.
Inactive ingredients (intravenous): arginine hydrochloride, histidine, histidine hydrochloride monohydrate, polysorbate 80, and water for injection.
Inactive ingredients (subcutaneous): arginine hydrochloride, histidine, histidine hydrochloride monohydrate, polysorbate 80, and water for injection.

Manufactured by:
Eisai Inc.
Nutley, NJ 07110
U.S. License No. 1862
LEQEMBI® is a registered trademark of Eisai R&D Management Co., Ltd.
LEQEMBI IQLIK™ is a trademark of Eisai R&D Management Co., Ltd.
© 2025 Eisai Inc. and Biogen
For more information, go to www.LEQEMBI.com or call 1-888-274-2378.

This Medication Guide has been approved by the U.S. Food and Drug Administration. Revised: 8/2025

INSTRUCTIONS FOR USE
LEQEMBI® IQLIK™ (le-KEM-bee)
(lecanemab-irmb)
360 mg/1.8 mL
injection, for subcutaneous use
single-dose prefilled autoinjector

This Instructions for Use contains information on how to prepare and use LEQEMBI IQLIK.

Before each use of LEQEMBI IQLIK
Read this Instructions for Use before you start using LEQEMBI IQLIK and each time you get a refill. There may be new information. This information does not take the place of talking to your healthcare provider about your medical condition or your treatment.
Your healthcare provider should show you or a caregiver how to use LEQEMBI IQLIK the right way before you use it for the first time. If you have any questions about how to use the autoinjector, contact your healthcare provider.

Important information

- LEQEMBI IQLIK is only given as an injection under the skin (subcutaneous).
- Do not remove the clear cap until you are ready to inject.
- Do not try to take apart the autoinjector at any time.
- Do not reuse the autoinjector.
- Do not inject through clothing.
- Do not shake the autoinjector.
- Do not use the autoinjector if the carton or any parts look damaged or has been dropped.
- Do not hold the autoinjector by the magenta needle cover.

Storing LEQEMBI IQLIK

- Store the LEQEMBI IQLIK autoinjector in a refrigerator between 36˚F to 46˚F (2˚C to 8°C).
- Do not freeze.
- Keep the LEQEMBI IQLIK autoinjector in the original package until ready to use, to protect it from light.
- LEQEMBI IQLIK may be stored at room temperature up to 77°F (25°C) for up to 14 days in the original package. Do not place it back in the refrigerator if it has been brought to room temperature.
- Do not shake LEQEMBI IQLIK.
- Throw away (dispose of) LEQEMBI IQLIK that is out of date, or if it is not stored the right way.
- Keep your LEQEMBI IQLIK autoinjector and all medicines out of the reach of children.

The LEQEMBI IQLIK autoinjector

Gather Supplies

Preparing to Inject LEQEMBI IQLIK

Step 1
Remove carton from the refrigerator and wait 20 minutes for the autoinjector to reach room temperature. Do not try to speed up the warming process in any way because the product may be damaged.
Check the carton.

- Do not use if the expiration date on the carton has passed.
- Do not use if the seal on the carton is broken.

Step 2
Check the autoinjector.

- Do not use if the autoinjector is damaged or has been dropped.

Check viewing window.

- Do not use if the medicine looks cloudy, discolored, or contains particles. The medicine should be clear and colorless to pale yellow. It is normal to see air bubbles in the window.

Check the expiration date.

- Do not use if the expiration date on the autoinjector has passed.

Step 3
Wash your hands with soap and water or use hand sanitizer.

Step 4
You can inject into the front of your thighs or stomach area (abdomen). If a caregiver gives you the injection, they may also do it in the back of your upper arm.

- Do not inject into moles, scars, bruises, tattoos or into areas where the skin is red, hard, tender or injured.
- Do not inject into the 2-inch area around the belly button.

Injecting LEQEMBI IQLIK

Step 5
Clean the injection site with an alcohol wipe and allow the skin to air dry.

- Do not touch the injection site after it is cleaned.
- Do not fan or blow on the cleaned area.

Step 6
Remove the clear cap when you are ready to inject.
Hold the autoinjector with 1 hand and firmly pull the clear cap straight off with your other hand.

- Do not bend or twist the clear cap while pulling it off.
- Do not put your fingers or hand over the needle. Doing this may cause a needle injury.
- Do not put back the clear cap on after it has been removed from the autoinjector.

Step 7
Throw away (dispose of) the cap in the household trash or sharps disposal container.

Step 8
Place the magenta needle cover at a 90-degree angle flat against the skin. Make sure you can see the viewing window.

- Do not inject through clothing.

Step 9
Push the autoinjector firmly against the skin to start the injection.
The injection will start automatically.

- You may hear a first “click” which indicates the start of the injection.
- The purple plunger rod will move down in the viewing window during the injection.

If you have trouble hearing the click, watch the purple plunger rod as it moves down.

Step 10
Continue holding the autoinjector down against the skin for about 10 seconds. You will hear a second click. The purple plunger rod will fill the viewing window.
Your injection is complete, but continue holding the autoinjector.

Step 11
Keep holding the autoinjector in place for at least 5 more seconds after the injection is complete.

Step 12
Remove the autoinjector by pulling it straight up from the injection site.

- The magenta needle cover will automatically move into place to cover the needle.

Step 13
You may notice a small drop of blood at the injection site. This is normal. Press a cotton ball or gauze on the area.

- If needed, cover the injection site with an adhesive bandage.
- Do not rub the injection site.

Step 14
Throw away (dispose of) the autoinjector in an FDA-cleared sharps disposal container.

Disposing of LEQEMBI IQLIK
Do not throw away (dispose of) the autoinjector in the household trash.
If you do not have an FDA-cleared sharps disposal container, you may use a household container that is:

- made of heavy-duty plastic,
- can be closed with a tight-fitting, puncture-resistant lid, without sharps being able to come out,
- upright and stable during use,
- leak-resistant, and
- properly labeled to warn of hazardous waste inside the container.

When your sharps disposal container is almost full, follow your community guidelines for the right way to throw away (dispose of) your sharps container. There may be state or local laws about how you should throw away used needles and syringes. For more information about safe sharps disposal, and for specific information about sharps disposal in the state that you live in, go to the FDA’s website at: http://www.fda.gov/safesharpsdisposal.
Do not dispose of your used sharps disposal container in your household trash unless your community guidelines permit this.
Do not recycle your used sharps disposal container.

Manufactured by.
Eisai Inc.
Nutley, NJ 07110
U.S. License No. 1862
LEQEMBI® is a registered trademark of Eisai R&D Management Co., Ltd.
LEQEMBI IQLIK™ is a trademark of Eisai R&D Management Co., Ltd.
© 2025 Eisai Inc. and Biogen
For more information, go to www.LEQEMBI.com or call 1-888-274-2378.
This Instructions for Use has been approved by the U.S. Food and Drug Administration.
Approved:8/2025

PACKAGE LABEL

PRINCIPAL DISPLAY PANEL

NDC 62856-215-01
LEQEMBI® (lecanemab-irmb)
injection
500 mg/5 mL
(100 mg/ mL)
Single-Dose Vial

PRINCIPAL DISPLAY PANEL

NDC 62856-215-01
LEQEMBI® (lecanemab-irmb)
injection
500 mg/5 mL
(100 mg/ mL)
Single-Dose Vial

PRINCIPAL DISPLAY PANEL

NDC 62856-212-01
LEQEMBI® (lecanemab-irmb)
injection
200 mg/2 mL
(100 mg/ mL)
1 vial per carton

PRINCIPAL DISPLAY PANEL

NDC 62856-220-01
LEQEMBI® lQLIK (lecanemab-irmb)
injection
360 mg/1.8 mL

PRINCIPAL DISPLAY PANEL

NDC 62856-220-10
Rx Only
LEQEMBI® lQLIK (lecanemab-irmb)
injection
360 mg/1.8 mL